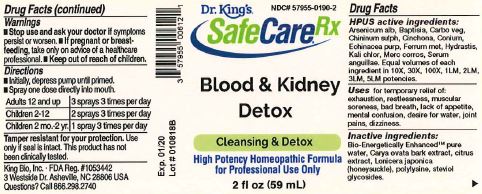 DRUG LABEL: Blood and Kidney Detox
NDC: 57955-0190 | Form: LIQUID
Manufacturer: King Bio Inc.
Category: homeopathic | Type: HUMAN OTC DRUG LABEL
Date: 20180214

ACTIVE INGREDIENTS: ARSENIC TRIOXIDE 10 [hp_X]/59 mL; BAPTISIA TINCTORIA ROOT 10 [hp_X]/59 mL; ACTIVATED CHARCOAL 10 [hp_X]/59 mL; QUININE SULFATE 10 [hp_X]/59 mL; CINCHONA OFFICINALIS BARK 10 [hp_X]/59 mL; CONIUM MACULATUM FLOWERING TOP 10 [hp_X]/59 mL; ECHINACEA PURPUREA 10 [hp_X]/59 mL; IRON 10 [hp_X]/59 mL; GOLDENSEAL 10 [hp_X]/59 mL; POTASSIUM CHLORATE 10 [hp_X]/59 mL; MERCURIC CHLORIDE 10 [hp_X]/59 mL; ANGUILLA ROSTRATA BLOOD SERUM 10 [hp_X]/59 mL
INACTIVE INGREDIENTS: WATER; CITRUS BIOFLAVONOIDS; LONICERA JAPONICA FLOWER; POLYEPSILON-LYSINE (4000 MW); REBAUDIOSIDE A

Blood and Kidney Detox™

ACTIVE INGREDIENT

Drug Facts__________________________________________________________________________________________________________

HPUS active ingredients: Arsenicum alb, Baptisia, Carbo veg, Chininum sulph, Cinchona, Conium, Echinacea purp, Ferrum met, Hydrastis, Kali chlor, Merc corros, Serum anguillae.

Equal volumes of each ingredient in 10X, 30X, 100X, 1LM, 2LM, 3LM, 5LM potencies.

INDICATIONS AND USAGE

Uses for temporary relief of: exhaustion, restlessness, muscular soreness, bad breath, lack of appetite, mental confusion, desire for water, joint pains, dizziness.

Inactive Ingredients:

Bio-Energetically Enhanced™ pure water, Carya ovata bark extract, citrus extract, Lonicera japonica (honeysuckle), polylysine, steviol glycosides.

Warnings

- Stop use and ask your doctor if symptoms persist or worsen.
- If pregnant or breast-feeding, take only on advice of a healthcare professional.

- Keep out of reach of children.

Directions

- Initially, depress pump until primed.
- Spray one dose directly into mouth.
- Adults 12 and up: 3 sprays 3 times per day
- Children 2-12: 2 sprays 3 times per day
- Children 2 mo.-2 yr.: 1 spray 3 times per day

OTHER SAFETY INFORMATION

Tamper resistant for your protection. Use only if safety seal is intact. This product has not been clinically tested.

PURPOSE

Uses for temporary relief of:

- exhaustion
- restlessness
- muscular soreness
- bad breath
- lack of appetite
- mental confusion
- desire for water
- joint pains
- dizziness